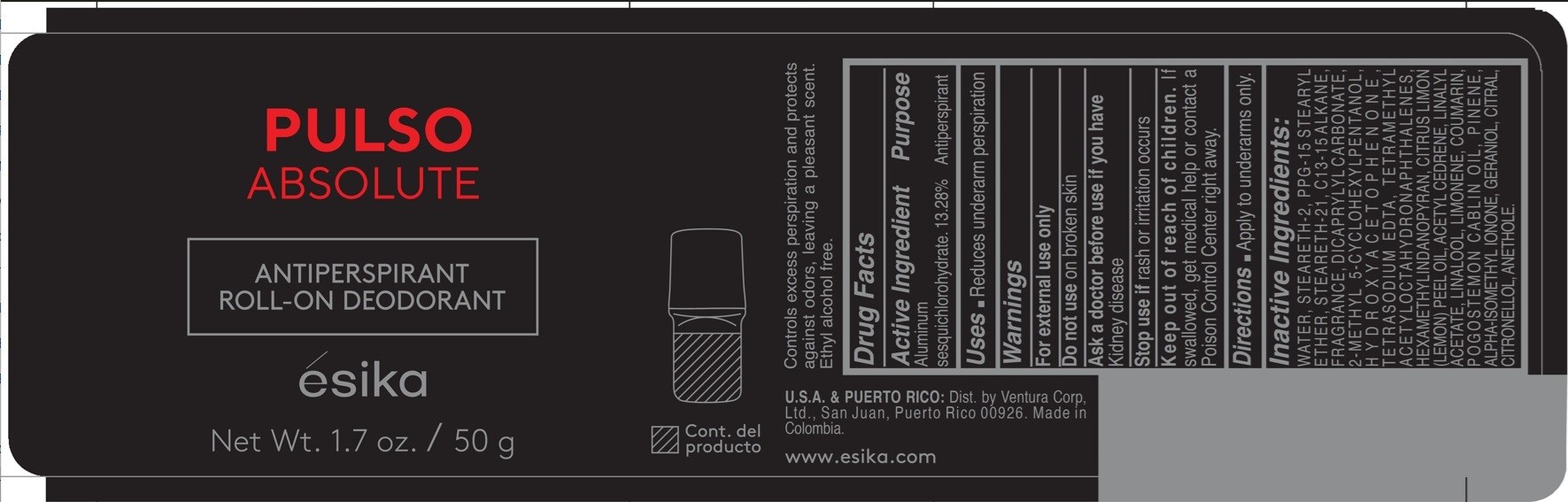 DRUG LABEL: Esika Pulso Absolute Antiperspirant Roll-on Deodorant
NDC: 14141-364 | Form: EMULSION
Manufacturer: Bel Star S.A.
Category: otc | Type: HUMAN OTC DRUG LABEL
Date: 20241204

ACTIVE INGREDIENTS: ALUMINUM SESQUICHLOROHYDRATE 132.8 mg/1 g
INACTIVE INGREDIENTS: ACETYL CEDRENE; LINALYL ACETATE; TETRAMETHYL ACETYLOCTAHYDRONAPHTHALENES; GERANIOL; CITRAL; CITRONELLOL; STEARETH-21; C13-15 ALKANE; HYDROXYACETOPHENONE; EDETATE SODIUM; COUMARIN; POGOSTEMON CABLIN OIL; LINALOOL, (+/-)-; STEARETH-2; PPG-15 STEARYL ETHER; LIMONENE, (+)-; DICAPRYLYL CARBONATE; ISOMETHYL-.ALPHA.-IONONE; WATER; ANETHOLE; 2-METHYL 5-CYCLOHEXYLPENTANOL; HEXAMETHYLINDANOPYRAN; CITRUS LIMON (LEMON) PEEL OIL; PINENE

Pulso Absolute Antiperspirant Roll-on Deodorant

Acitve Ingredient

Aluminum sesquichlorohydrate 13.28%

Purpose

Antiperspirant

Uses

- Reduces underarm perspiration

Warnings

For external use only

Do not use

on broken skin

Ask a doctor before use if you have

kidney disease

Stop use if

rash or irritation occurs

Keep out of reach of children.

If swallowed, get medical help or contact a Poison Control Center right away.

Directions

- Apply to underarms only.

Inactive Ingredients

WATER, STEARETH-2, PPG-15 STEARYL ETHER, STEARETH-21, C13-15 ALKANE, FRAGRANCE, DICAPRYLYL CARBONATE, 2-METHYL 5-CYCLOHEXYLPENTANOL, HYDROXYACETOPHENONE, TETRASODIUM EDTA, TETRAMETHYL ACETYLOCTAHYDRONAPHTHALENES, HEXAMETHYLINDANOPYRAN, CITRUS LIMON (LEMON) PEEL OIL, ACETYL CEDRENE, LINALYL ACETATE, LINALOOL, LIMONENE, COUMARIN, POGOSTEMON CABLIN OIL, PINENE, ALPHA-ISOMETHYL IONONE, GERANIOL, CITRAL, CITRONELLOL, ANETHOLE.

Company Information

Dist. by Ventura Corp, Ltd., San Juan, Puerto Rico 00926

Made in Colombia.

www.esika.com